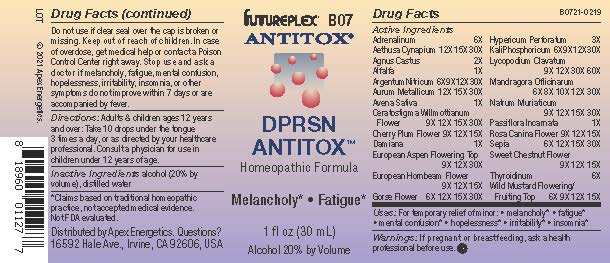 DRUG LABEL: B07
NDC: 63479-0207 | Form: SOLUTION/ DROPS
Manufacturer: Apex Energetics Inc.
Category: homeopathic | Type: HUMAN OTC DRUG LABEL
Date: 20240108

ACTIVE INGREDIENTS: CHASTE TREE 2 [hp_X]/1 mL; AVENA SATIVA FLOWERING TOP 1 [hp_X]/1 mL; CARPINUS BETULUS FLOWER 15 [hp_X]/1 mL; CASTANEA SATIVA FLOWER 15 [hp_X]/1 mL; THYROID, UNSPECIFIED 6 [hp_X]/1 mL; TURNERA DIFFUSA LEAFY TWIG 1 [hp_X]/1 mL; POPULUS TREMULA FLOWERING TOP 30 [hp_X]/1 mL; ULEX EUROPAEUS FLOWER 30 [hp_X]/1 mL; SODIUM CHLORIDE 30 [hp_X]/1 mL; PASSIFLORA INCARNATA FLOWERING TOP 1 [hp_X]/1 mL; SEPIA OFFICINALIS JUICE 30 [hp_X]/1 mL; GOLD 30 [hp_X]/1 mL; EPINEPHRINE 6 [hp_X]/1 mL; PRUNUS CERASIFERA FLOWER 15 [hp_X]/1 mL; HYPERICUM PERFORATUM 3 [hp_X]/1 mL; POTASSIUM PHOSPHATE, DIBASIC 30 [hp_X]/1 mL; MANDRAGORA OFFICINARUM ROOT 30 [hp_X]/1 mL; LYCOPODIUM CLAVATUM SPORE 60 [hp_X]/1 mL; ROSA CANINA FLOWER 15 [hp_X]/1 mL; SINAPIS ARVENSIS FLOWERING/FRUITING TOP 15 [hp_X]/1 mL; AETHUSA CYNAPIUM 30 [hp_X]/1 mL; ALFALFA 1 [hp_X]/1 mL; SILVER NITRATE 30 [hp_X]/1 mL; CERATOSTIGMA WILLMOTTIANUM FLOWER 30 [hp_X]/1 mL
INACTIVE INGREDIENTS: ALCOHOL; WATER

B07

Active Ingredients
Adrenalinum | 6X
Aethusa Cynapium | 12X 15X 30X
Agnus Castus | 2X
Alfalfa | 1X
Argentum Nitricum | 6X 9X 12X 30X
Aurum Metallicum | 12X 15X 30X
Avena Sativa | 1X
Ceratostigma Willmottianum Flower | 9X 12X 15X 30X
Cherry Plum Flower | 9X 12X 15X
Damiana | 1X
European Aspen Flowering Top | 9X 12X 30X
European Hornbeam Flower | 9X 12X 15X
Gorse Flower | 6X 12X 15X 30X
Hypericum Perforatum | 3X
Kali Phosphoricum | 6X 9X 12X 30X
Lycopodium Clavatum | 9X 12X 30X 60X
Mandragora Officinarum | 6X 8X 10X 12X 30X
Natrum Muriaticum | 9X 12X 15X 30X
Passiflora Incarnata | 1X
Rosa Canina Flower | 9X 12X 15X
Sepia | 6X 12X 15X 30X
Sweet Chestnut Flower | 9X 12X 15X
Thyroidinum | 6X
Wild Mustard Flowering/Fruiting Top | 6X 9X 12X 15X

Uses:

PURPOSE

For temporary relief of minor:

melancholy*

fatigue*

mental confusion*

hopelessness*

irritability*

insomnia*

*Claims based on traditional homeopathic practice, not accepted medical evidence. Not FDA evaluated.

Warnings:

PREGNANCY OR BREAST FEEDING

If pregnant or breastfeeding, ask a health professional before use.

Do not use if clear seal over the cap is broken or missing.

Keep out of reach of children. In case of overdose, get medical help or contact a Poison Control Center right away.

Stop use and ask a doctor if melancholy, fatigue, mental confusion, hopelessness, irritability, insomnia, or other symptoms do not improve within 7 days or are accompanied by fever.

Directions:

Adults & children ages 12 years and over: Take 10 drops under the tongue 3 times a day, or as directed by your healthcare professional. Consult a physician for use in children under 12 years of age.

Inactive Ingredients

alcohol (20% by volume), distilled water

Distributed by Apex Energetics. Questions?

16592 Hale Ave., Irvine, CA 92606, USA

PACKAGE LABEL

FUTUREPLEX® B07

ANTITOX®

DPRSN ANTITOX™

Homeopathic Formula

Melancholy*

Fatigue*

1 fl oz (30 mL)

Alcohol 20% by Volume